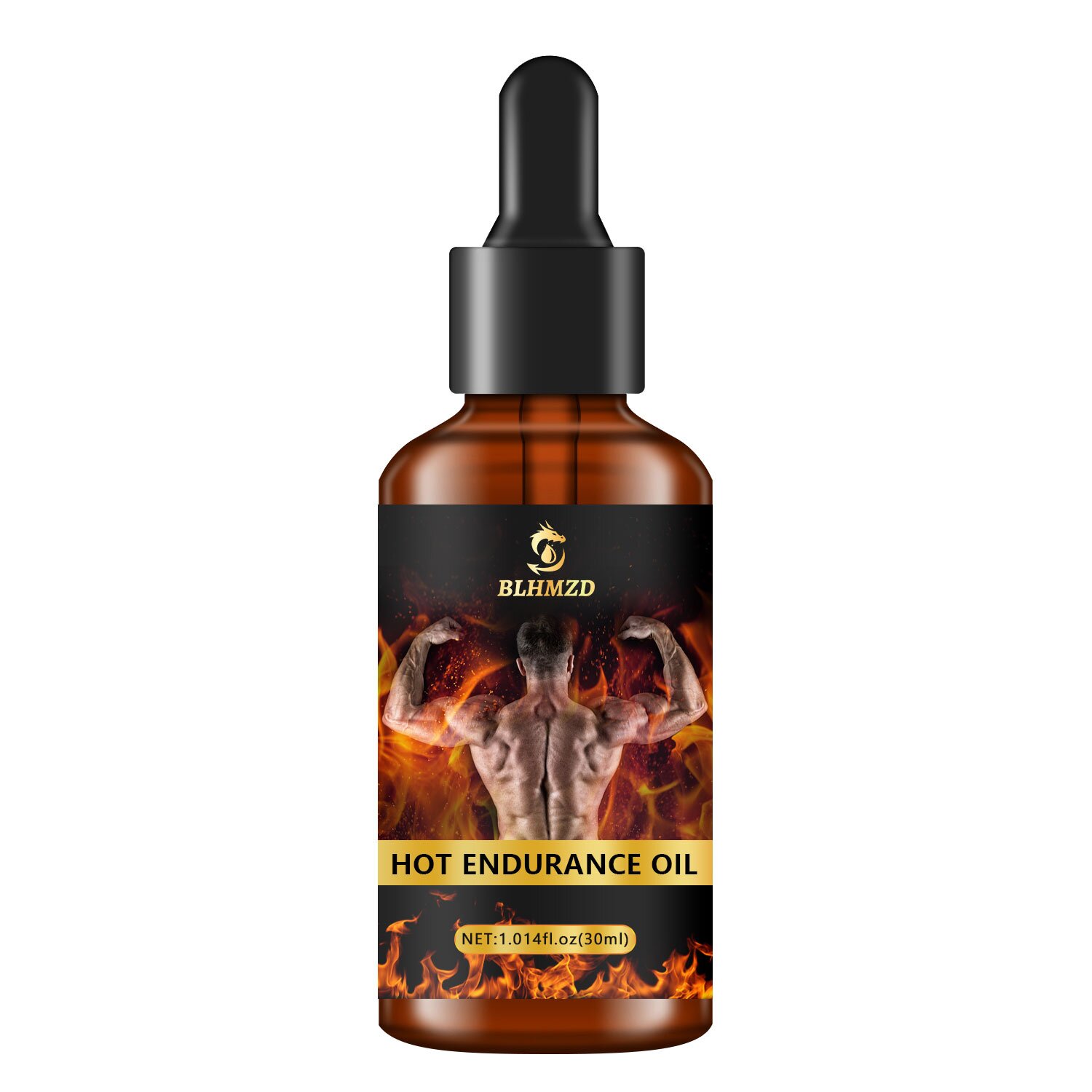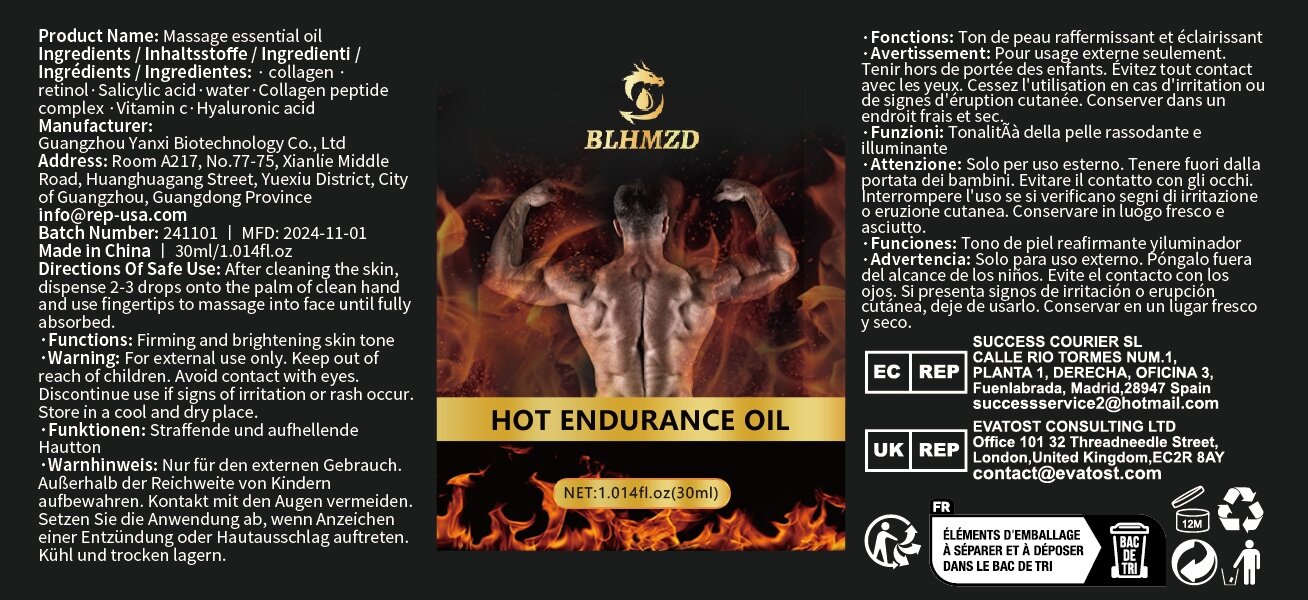 DRUG LABEL: Massage essential oil
NDC: 84025-317 | Form: OIL
Manufacturer: Guangzhou Yanxi Biotechnology Co., Ltd
Category: otc | Type: HUMAN OTC DRUG LABEL
Date: 20250107

ACTIVE INGREDIENTS: HYALURONIC ACID 3 mg/100 mL; RETINOL 5 mg/100 mL
INACTIVE INGREDIENTS: WATER

DOSAGE AND ADMINISTRATION

After cleaning the skin,dispense 2-3 drops onto the palm of clean handand use fingertips to massage into face until fully absorbed.

WARNINGS

Keep out of children

INACTIVE INGREDIENT

Aqua

INDICATIONS AND USAGE

for body care

keep out of children

PURPOSE

Moisturize and hydrate the skin